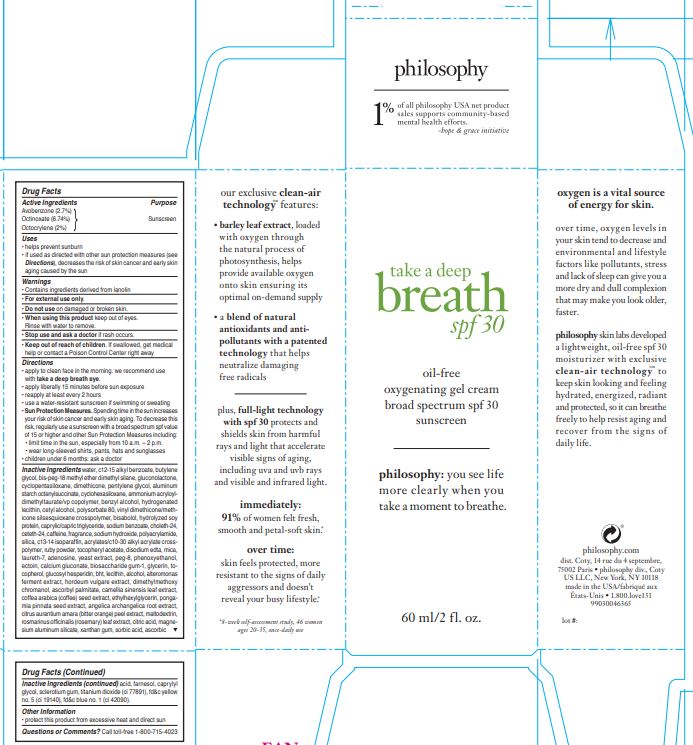 DRUG LABEL: take a deep breath spf 30
NDC: 50184-1065 | Form: CREAM
Manufacturer: Philosophy Inc.
Category: otc | Type: HUMAN OTC DRUG LABEL
Date: 20190107

ACTIVE INGREDIENTS: AVOBENZONE 2.7 g/100 mL; OCTINOXATE 6.74 g/100 mL; OCTOCRYLENE 2 g/100 mL
INACTIVE INGREDIENTS: WATER

Active Ingredients

Avobenzone (2.7%) Octinoxate (6.74%) Octocrylene (2%)

Purpose

Sunscreen

Uses

helps prevent sunburn • if used as directed with other sun protection measures (see Directions), decreases the risk of skin cancer and early skin aging caused by the sun

Warnings

• Contains ingredients derived from lanolin • For external use only

Do not use

on damaged or broken skin.

When using this product

keep out of eyes. Rinse with water to remove.

Stop use and ask a doctor

if rash occurs.

Keep out of reach of children.

If swallowed, get medical help or contact a Poison Control Center right away.

Directions

• apply to clean face in the morning. we recommend use with take a deep breath eye. • apply liberally 15 minutes before sun exposure • reapply at least every 2 hours • use a water-resistant sunscreen if swimming or sweating • Sun Protection Measures. Spending time in the sun increases your risk of skin cancer and early skin aging. To decrease this risk, regularly use a sunscreen with a broad spectrum spf value of 15 or higher and other Sun Protection Measures including: • limit time in the sun, especially from 10 a.m. – 2 p.m. • wear long-sleeved shirts, pants, hats and sunglasses • children under 6 months: ask a doctor

Inactive Ingredients

s water, c12-15 alkyl benzoate, butylene glycol, bis-peg-18 methyl ether dimethyl silane, gluconolactone, cyclopentasiloxane, dimethicone, pentylene glycol, aluminum starch octenylsuccinate, cyclohexasiloxane, ammonium acryloyldimethyltaurate/vp copolymer, benzyl alcohol, hydrogenated lecithin, cetyl alcohol, polysorbate 80, vinyl dimethicone/methicone silsesquioxane crosspolymer, bisabolol, hydrolyzed soy protein, caprylic/capric triglyceride, sodium benzoate, choleth-24, ceteth-24, caffeine, fragrance, sodium hydroxide, polyacrylamide, silica, c13-14 isoparaffin, acrylates/c10-30 alkyl acrylate crosspolymer, ruby powder, tocopheryl acetate, disodium edta, mica, laureth-7, adenosine, yeast extract, peg-8, phenoxyethanol, ectoin, calcium gluconate, biosaccharide gum-1, glycerin, tocopherol, glucosyl hesperidin, bht, lecithin, alcohol, alteromonas ferment extract, hordeum vulgare extract, dimethylmethoxy chromanol, ascorbyl palmitate, camellia sinensis leaf extract, coffea arabica (coffee) seed extract, ethylhexylglycerin, pongamia pinnata seed extract, angelica archangelica root extract, citrus aurantium amara (bitter orange) peel extract, maltodextrin, rosmarinus officinalis (rosemary) leaf extract, citric acid, magnesium aluminum silicate, xanthan gum, sorbic acid, ascorbic acid, farnesol, caprylyl glycol, sclerotium gum, titanium dioxide (ci 77891), fd&c yellow no. 5 (ci 19140), fd&c blue no. 1 (ci 42090).

Other information

• protect this product from excessive heat and direct sun.

Questions or Comments?

Call toll-free 1-800-715-4023

Principal Display Panel

take a deep

breath

spf 30

oil-free

oxygenating gel cream

broad spectrum spf 30

sunscreen

philosophy: you see life

more clearly when you

take a moment to breathe.

60 ml/2 fl.oz.